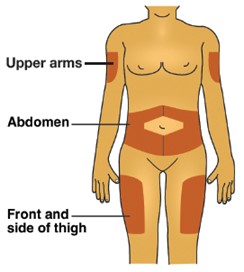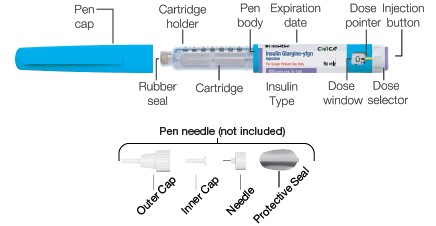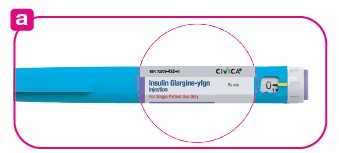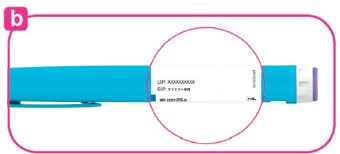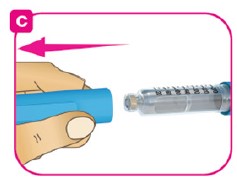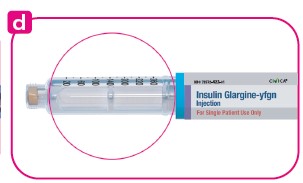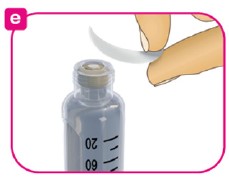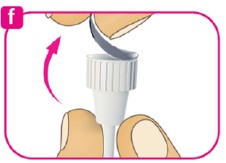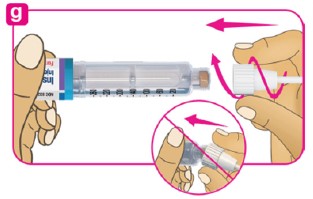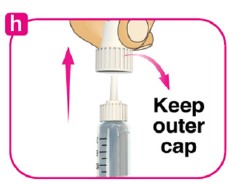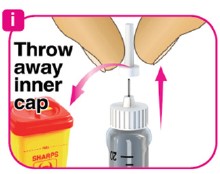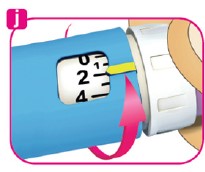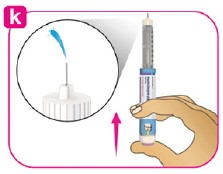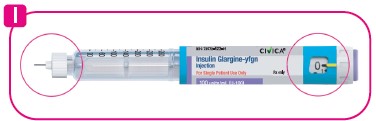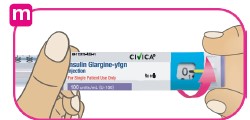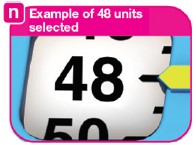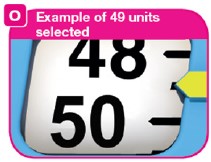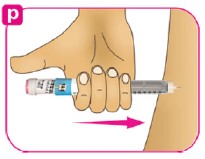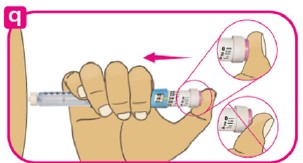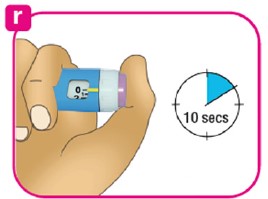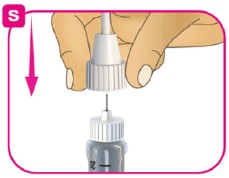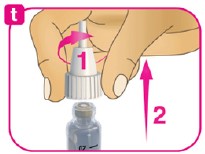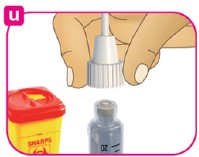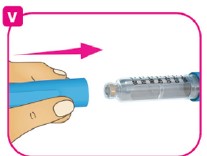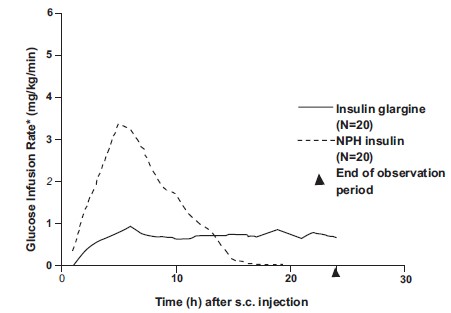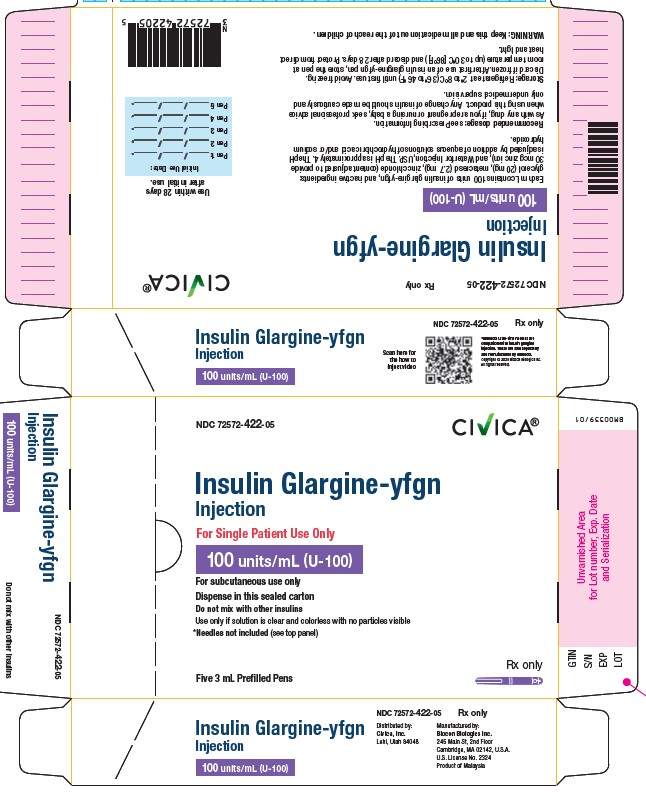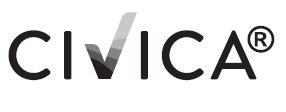 DRUG LABEL: INSULIN GLARGINE 
NDC: 72572-422 | Form: INJECTION, SOLUTION
Manufacturer: Civica, Inc. 
Category: prescription | Type: HUMAN PRESCRIPTION DRUG LABEL
Date: 20250724

ACTIVE INGREDIENTS: INSULIN GLARGINE 100 [iU]/1 mL
INACTIVE INGREDIENTS: ZINC CHLORIDE 30 ug/1 mL; GLYCERIN 20 mg/1 mL; METACRESOL 2.7 mg/1 mL; WATER; HYDROCHLORIC ACID; SODIUM HYDROXIDE

HIGHLIGHTS OF PRESCRIBING INFORMATION

These highlights do not include all the information needed to use INSULIN GLARGINE-YFGN safely and effectively. See full prescribing information for INSULIN GLARGINE-YFGN.
INSULIN GLARGINE-YFGN injection, for subcutaneous use
Initial U.S. Approval: 2021
Insulin glargine-yfgn is a biosimilar* to LANTUS (insulin glargine).

1 INDICATIONS AND USAGE

Insulin Glargine-yfgn is a long-acting human insulin analog indicated to improve glycemic control in adult and pediatric patients with diabetes mellitus. (1)

Limitations of Use

Not recommended for the treatment of diabetic ketoacidosis. (1)

2 DOSAGE AND ADMINISTRATION

- Individualize dosage based on metabolic needs, blood glucose monitoring, glycemic control, type of diabetes, and prior insulin use. (2.2)
- Administer subcutaneously into the abdominal area, thigh, or deltoid once daily at any time of day, but at the same time every day. (2.1)
- Do not dilute or mix with any other insulin or solution. (2.1)
- Rotate injection sites to reduce risk of lipodystrophy and localized cutaneous amyloidosis. (2.1)
- See Full Prescribing Information for the recommended starting dosage in patients with type 2 diabetes (2.3) and how to change to Insulin Glargine-yfgn from other insulins. (2.4)
- Closely monitor glucose when switching to Insulin Glargine-yfgn and during initial weeks thereafter. (2.4)

3 DOSAGE FORMS AND STRENGTHS

Injection: 100 units/mL (U-100) available as:

- 3 mL single-patient-use prefilled pen (3)

4 CONTRAINDICATIONS

- During episodes of hypoglycemia (4)
- Hypersensitivity to insulin glargine products or any excipient in Insulin Glargine-yfgn (4)

5 WARNINGS AND PRECAUTIONS

- Never share an Insulin Glargine-yfgn prefilled pen, insulin syringe, or needle between patients, even if the needle is changed. (5.1)
- Hyperglycemia or hypoglycemia with changes in insulin regimen: Make changes to a patient’s insulin regimen (e.g., insulin strength, manufacturer, type, injection site or method of administration) under close medical supervision with increased frequency of blood glucose monitoring. (5.2)
- Hypoglycemia: May be life-threatening. Increase frequency of glucose monitoring with changes to: insulin dosage, concomitant drugs, meal pattern, physical activity; and in patients with renal or hepatic impairment and hypoglycemia unawareness. (5.3)
- Hypoglycemia due to medication errors: Accidental mix-ups between insulin products can occur. Instruct patients to check insulin labels before injection. (5.4)
- Hypersensitivity reactions: Severe, life-threatening, generalized allergy, including anaphylaxis, can occur. Discontinue Insulin Glargine-yfgn. Monitor and treat if indicated. (5.5)
- Hypokalemia: May be life-threatening. Monitor potassium levels in patients at risk of hypokalemia and treat if indicated. (5.6)
- Fluid retention and heart failure with concomitant use of thiazolidinediones (TZDs): Observe for signs and symptoms of heart failure; consider dosage reduction or discontinuation of TZD if heart failure occurs. (5.7)

6 ADVERSE REACTIONS

Adverse reactions commonly associated with insulin glargine products include hypoglycemia, allergic reactions, injection site reactions, lipodystrophy, pruritus, rash, edema, and weight gain. (6.1)

To report SUSPECTED ADVERSE REACTIONS, contact Biocon Biologics at 1-833-986-1468 or FDA at 1-800-FDA-1088 or www.fda.gov/medwatch.

7 DRUG INTERACTIONS

- Drugs that Affect Glucose Metabolism: Adjustment of insulin dosage may be needed. (7)
- Antiadrenergic Drugs (e.g., beta-blockers, clonidine, guanethidine, and reserpine): Signs and symptoms of hypoglycemia may be reduced or absent. (7)

* Biosimilar means that the biological product is approved based on data demonstrating that it is highly similar to an FDA-approved biological product, known as a reference product, and that there are no clinically meaningful differences between the biosimilar product and the reference product. Biosimilarity of Insulin Glargine-yfgn has been demonstrated for the condition(s) of use (e.g., indication(s), dosing regimen(s)), strength(s), dosage form(s), and route(s) of administration described in its Full Prescribing Information.

FULL PRESCRIBING INFORMATION

1 INDICATIONS AND USAGE

Insulin Glargine-yfgn is indicated to improve glycemic control in adult and pediatric patients with diabetes mellitus.

Limitations of Use

Insulin Glargine-yfgn is not recommended for the treatment of diabetic ketoacidosis.

2 DOSAGE AND ADMINISTRATION

2.1 Important Administration Instructions

- Always check insulin labels before administration. This product is Insulin Glargine-yfgn [see Warnings and Precautions (5.4)].
- Visually inspect Insulin Glargine-yfgn vials and prefilled pens for particulate matter and discoloration prior to administration. Only use if the solution is clear and colorless with no visible particles.
- Administer Insulin Glargine-yfgn subcutaneously into the abdominal area, thigh, or deltoid, and rotate injection sites within the same region from one injection to the next to reduce the risk of lipodystrophy and localized cutaneous amyloidosis. Do not inject into areas of lipodystrophy or localized cutaneous amyloidosis [see Warnings and Precautions (5.2), and Adverse Reactions (6)].
- During changes to a patient’s insulin regimen, increase the frequency of blood glucose monitoring [see Warnings and Precautions (5.2)].
- Do not administer intravenously or via an insulin pump.
- Do not dilute or mix Insulin Glargine-yfgn with any other insulin or solution.
- The Insulin Glargine-yfgn prefilled pen dials in 1-unit increments.
- Use the Insulin Glargine-yfgn prefilled pen with caution in patients with visual impairment who may rely on audible clicks to dial their dose.

2.2 General Dosing Instructions

- Administer Insulin Glargine-yfgn subcutaneously once daily at any time of day but at the same time every day.
- Individualize and adjust the dosage of Insulin Glargine-yfgn based on the patient’s metabolic needs, blood glucose monitoring results and glycemic control goal.
- Dosage adjustments may be needed with changes in physical activity, changes in meal patterns (i.e., macronutrient content or timing of food intake), during acute illness, or changes in renal or hepatic function. Dosage adjustments should only be made under medical supervision with appropriate glucose monitoring [see Warnings and Precautions (5.2)].
- In patients with type 1 diabetes, Insulin Glargine-yfgn must be used concomitantly with short-acting insulin.

2.3 Initiation of Insulin Glargine-yfgn Therapy

Recommended Starting Dosage in Patients with Type 1 Diabetes
The recommended starting dosage of Insulin Glargine-yfgn in patients with type 1 diabetes is approximately one-third of the total daily insulin requirements. Use short-acting, premeal insulin to satisfy the remainder of the daily insulin requirements

Recommended Starting Dosage in Patients with Type 2 Diabetes
The recommended starting dosage of Insulin Glargine-yfgn in patients with type 2 diabetes who are not currently treated with insulin is 0.2 units/kg or up to 10 units once daily.

2.4 Switching to Insulin Glargine-yfgn from Other Insulin Therapies

Dosage adjustments are recommended to lower the risk of hypoglycemia when switching patients to Insulin Glargine-yfgn from other insulin therapies [see Warnings and Precautions (5.3)]. When switching from:

- Once-daily insulin glargine 300 units/mL to once-daily Insulin Glargine-yfgn (100 units/mL), the recommended starting Insulin Glargine-yfgn dosage is 80% of the insulin glargine, 300 units/mL dosage that is being discontinued.
- Once-daily NPH insulin to once-daily Insulin Glargine-yfgn, the recommended starting Insulin Glargine-yfgn dosage is the same as the dosage of NPH that is being discontinued.
- Twice-daily NPH insulin to once-daily Insulin Glargine-yfgn, the recommended starting Insulin Glargine-yfgn dosage is 80% of the total NPH dosage that is being discontinued.

3 DOSAGE FORMS AND STRENGTHS

Injection: 100 units/mL (U-100) a clear and colorless solution available as:

- 3 mL single-patient-use prefilled pen

4 CONTRAINDICATIONS

Insulin Glargine-yfgn is contraindicated:

- During episodes of hypoglycemia [see Warnings and Precautions (5.3)].
- In patients with hypersensitivity to insulin glargine products or any of the excipients in Insulin Glargine-yfgn [see Warnings and Precautions (5.5)].

5 WARNINGS AND PRECAUTIONS

5.1 Never Share an Insulin Glargine-yfgn Prefilled Pen, Insulin Syringe, or Needle Between Patients

Insulin Glargine-yfgn prefilled pens must never be shared between patients, even if the needle is changed. Patients using Insulin Glargine-yfgn vials must never re-use or share needles or syringes with another person. Sharing poses a risk for transmission of blood-borne pathogens.

5.2 Hyperglycemia or Hypoglycemia with Changes in Insulin Regimen

Changes in an insulin regimen (e.g., insulin strength, manufacturer, type, injection site or method of administration) may affect glycemic control and predispose to hypoglycemia [see Warnings and Precautions (5.3)] or hyperglycemia. Repeated insulin injections into areas of lipodystrophy or localized cutaneous amyloidosis have been reported to result in hyperglycemia; and a sudden change in the injection site (to unaffected area) has been reported to result in hypoglycemia [see Adverse Reactions (6)].

Make any changes to a patient’s insulin regimen under close medical supervision with increased frequency of blood glucose monitoring. Advise patients who have repeatedly injected into areas of lipodystrophy or localized cutaneous amyloidosis to change the injection site to unaffected areas and closely monitor for hypoglycemia. For patients with type 2 diabetes, dosage adjustments of concomitant oral and antidiabetic products may be needed.

5.3 Hypoglycemia

Hypoglycemia is the most common adverse reaction associated with insulins, including insulin glargine products. Severe hypoglycemia can cause seizures, may be life-threatening or cause death. Hypoglycemia can impair concentration ability and reaction time; this may place the patient and others at risk in situations where these abilities are important (e.g., driving or operating other machinery).

Hypoglycemia can happen suddenly, and symptoms may differ in each patient and change over time in the same patient. Symptomatic awareness of hypoglycemia may be less pronounced in patients with longstanding diabetes, in patients with diabetic neuropathy, using drugs that block the sympathetic nervous system (e.g., beta-blockers) [see Drug Interactions (7)], or who experience recurrent hypoglycemia.

The long-acting effect of insulin glargine products may delay recovery from hypoglycemia.

Risk Factors for Hypoglycemia

The risk of hypoglycemia after an injection is related to the duration of action of the insulin and, in general, is highest when the glucose lowering effect of the insulin is maximal. As with all insulins, the glucose lowering effect time course of insulin glargine products may vary in different patients or at different times in the same patient and depends on many conditions, including the area of injection as well as the injection site blood supply and temperature [ see Clinical Pharmacology (12.2)]. Other factors which may increase the risk of hypoglycemia include changes in meal pattern (e.g., macronutrient content or timing of meals), changes in level of physical activity, or changes to concomitant drugs [ see Drug Interactions (7)]. Patients with renal or hepatic impairment may be at higher risk of hypoglycemia [see Use in Specific Populations (8.6, 8.7)].

Risk Mitigation Strategies for Hypoglycemia

Patients and caregivers must be educated to recognize and manage hypoglycemia. Self-monitoring of blood glucose plays an essential role in the prevention and management of hypoglycemia. In patients at higher risk for hypoglycemia and patients who have reduced symptomatic awareness of hypoglycemia, increased frequency of blood glucose monitoring is recommended.

5.4 Hypoglycemia Due to Medication Errors

Accidental mix-ups among insulin products have been reported. To avoid medication errors between Insulin Glargine-yfgn and other insulins, instruct patients to always check the insulin label before each injection [see Adverse Reactions (6.3)].

5.5 Hypersensitivity Reactions

Severe, life-threatening, generalized allergy, including anaphylaxis, can occur with insulins, including insulin glargine products [see Adverse Reactions (6.1)] . If hypersensitivity reactions occur, discontinue Insulin Glargine-yfgn; treat per standard of care and monitor until symptoms and signs resolve. Insulin Glargine-yfgn is contraindicated in patients who have had hypersensitivity reactions to insulin glargine products or one of the excipients.

5.6 Hypokalemia

All insulins, including insulin glargine products, cause a shift in potassium from the extracellular to intracellular space, possibly leading to hypokalemia. Untreated hypokalemia may cause respiratory paralysis, ventricular arrhythmia, and death. Monitor potassium levels in patients at risk for hypokalemia, if indicated (e.g., patients using potassium-lowering medications, patients taking medications sensitive to serum potassium concentrations).

5.7 Fluid Retention and Heart Failure with Concomitant Use of PPAR-gamma Agonists

Thiazolidinediones (TZDs), which are peroxisome proliferator-activated receptor (PPAR)-gamma agonists, can cause dose-related fluid retention, when used in combination with insulin. Fluid retention may lead to or exacerbate heart failure. Patients treated with insulin, including Insulin Glargine-yfgn, and a PPAR-gamma agonist should be observed for signs and symptoms of heart failure. If heart failure develops, it should be managed according to current standards of care, and discontinuation or dose reduction of the PPAR-gamma agonist must be considered.

6 ADVERSE REACTIONS

The following adverse reactions are discussed elsewhere:

- Hyperglycemia or Hypoglycemia with Changes in Insulin Regimen [see Warnings and Precautions (5.2)]
- Hypoglycemia [see Warnings and Precautions (5.3)]
- Hypoglycemia Due to Medication Errors [see Warnings and Precautions (5.4)]
- Hypersensitivity Reactions [see Warnings and Precautions (5.5)]
- Hypokalemia [see Warnings and Precautions (5.6)]

6.1 Clinical Trials Experience

Because clinical trials are conducted under widely varying conditions, adverse reaction rates observed in clinical trials of a drug cannot be directly compared to rates in the clinical trial of another drug and may not reflect the rates observed in practice.

The data in Table 1 reflect the exposure of 2,327 patients with type 1 diabetes to insulin glargine or NPH in Studies A, B, C, and D [see Clinical Studies (14.2)]. The type 1 diabetes population had the following characteristics: the mean age was 39 years, 54% were male and the mean body mass index (BMI) was 25.1 kg/m^2. Ninety-seven percent were White, 2% were Black or African American and less than 1% were Asian. Approximately 3% of the patients in studies B and C were Hispanic.

The data in Table 2 reflect the exposure of 1,563 patients with type 2 diabetes to insulin glargine or NPH in Studies E, F, and G [see Clinical Studies (14.3)]. The type 2 diabetes population had the following characteristics: the mean age was 59 years, 58% were male, and the mean BMI was 29.2 kg/m^2. Eighty-seven percent were White, 8% were Black or African American, and 3% were Asian. Approximately 9% of patients in Study F were Hispanic.

The frequencies of adverse reactions during insulin glargine clinical studies in patients with type 1 diabetes mellitus and type 2 diabetes mellitus are listed in the tables below (Tables 1, 2, 3, and 4).

Table 1: Adverse Reactions Occurring ≥ 5% in Pooled Clinical Studies up to 28 Weeks Duration in Adults with Type 1 Diabetes
 | Insulin Glargine, %; (n = 1,257) | NPH,%; (n = 1,070)
Upper respiratory tract infection | 22.4 | 23.1
Infection [Body system not specified] | 9.4 | 10.3
Accidental injury | 5.7 | 6.4
Headache | 5.5 | 4.7

Table 2: Adverse Reactions Occurring ≥ 5% in Pooled Clinical Studies up to 1 Year Duration in Adults with Type 2 Diabetes
 | Insulin Glargine, %; (n = 849) | NPH,%; (n = 714)
Upper respiratory tract infection | 11.4 | 13.3
Infection [Body system not specified] | 10.4 | 11.6
Retinal vascular disorder | 5.8 | 7.4

Table 3: Adverse Reactions Occurring ≥ 10% in a 5-Year Study of Adults with Type 2 Diabetes
 | Insulin Glargine, %; (n = 514) | NPH,%; (n = 503)
Upper respiratory tract infection | 29.0 | 33.6
Edema peripheral | 20.0 | 22.7
Hypertension | 19.6 | 18.9
Influenza | 18.7 | 19.5
Sinusitis | 18.5 | 17.9
Cataract | 18.1 | 15.9
Bronchitis | 15.2 | 14.1
Arthralgia | 14.2 | 16.1
Pain in extremity | 13.0 | 13.1
Back pain | 12.8 | 12.3
Cough | 12.1 | 7.4
Urinary tract infection | 10.7 | 10.1
Diarrhea | 10.7 | 10.3
Depression | 10.5 | 9.7
Headache | 10.3 | 9.3

Table 4: Adverse Reactions Occurring ≥ 5% in a 28-Week Clinical Study in Pediatric Patients with Type 1 Diabetes
 | Insulin Glargine, %; (n = 174) | NPH,%; (n = 175)
Infection [Body system not specified] | 13.8 | 17.7
Upper respiratory tract infection | 13.8 | 16.0
Pharyngitis | 7.5 | 8.6
Rhinitis | 5.2 | 5.1

Severe Hypoglycemia

Hypoglycemia was the most commonly observed adverse reaction in patients treated with insulin glargine. Tables 5, 6, and 7 summarize the incidence of severe hypoglycemia in the insulin glargine clinical studies. Severe symptomatic hypoglycemia was defined as an event with symptoms consistent with hypoglycemia requiring the assistance of another person and associated with either a blood glucose below 50 mg/dL (≤ 56 mg/dL in the 5-year study and ≤ 36 mg/dL in the ORIGIN study) or prompt recovery after oral carbohydrate, intravenous glucose, or glucagon administration.

Percentages of insulin glargine-treated adult patients who experienced severe symptomatic hypoglycemia in the insulin glargine clinical studies [see Clinical Studies (14)] were comparable to percentages of NPH-treated patients for all treatment regimens (see Tables 5 and 6). In the pediatric clinical study, pediatric patients with type 1 diabetes had a higher incidence of severe symptomatic hypoglycemia in the two treatment groups compared to the adult studies with type 1 diabetes.

Table 5: Severe Symptomatic Hypoglycemia in Patients with Type 1 Diabetes
 | Study A; Type 1 Diabetes; Adults; 28 weeks; In combination with; regular insulin |  | Study B; Type 1 Diabetes; Adults; 28 weeks; In combination with; regular insulin |  | Study C; Type 1 Diabetes; Adults; 16 weeks; In combination with insulin; lispro |  | Study D; Type 1 Diabetes; Pediatrics; 26 weeks; In combination with; regular insulin
 | Insulin Glargine; n = 292 | NPH; n = 293 | Insulin Glargine; n = 264 | NPH; n = 270 | Insulin Glargine; n = 310 | NPH; n = 309 | Insulin Glargine; n = 174 | NPH; n = 175
Percent of patients | 10.6 | 15.0 | 8.7 | 10.4 | 6.5 | 5.2 | 23.0 | 28.6

Table 6: Severe Symptomatic Hypoglycemia in Patients with Type 2 Diabetes
 | Study E; Type 2 Diabetes; Adults; 52 weeks; In combination with; oral agents |  | Study F; Type 2 Diabetes; Adults; 28 weeks; In combination with regular insulin |  | Study G; Type 2 Diabetes; Adults; 5 years; In combination with regular insulin
 | Insulin Glargine; n = 289 | NPH; n = 281 | Insulin Glargine; n = 259 | NPH; n = 259 | Insulin Glargine; n = 513 | NPH; n = 504
Percent of patients | 1.7 | 1.1 | 0.4 | 2.3 | 7.8 | 11.9

Table 7 displays the proportion of patients who experienced severe symptomatic hypoglycemia in the insulin glargine and Standard Care groups in the ORIGIN study [see Clinical Studies (14)].

Table 7: Severe Symptomatic Hypoglycemia in the ORIGIN Study
 | ORIGIN Study; Median duration of follow-up: 6.2 years
 | Insulin Glargine; n = 6231 | Standard Care; n = 6273
Percent of patients | 5.6 | 1.8

Peripheral Edema

Some patients taking insulin glargine products have experienced sodium retention and edema, particularly if previously poor metabolic control was improved by intensified insulin therapy.

Lipodystrophy

Administration of insulin subcutaneously, including insulin glargine products, has resulted in lipoatrophy (depression in the skin) or lipohypertrophy (enlargement or thickening of tissue) in some patients [see Dosage and Administration (2.2)].

Insulin Initiation and Intensification of Glucose Control

Intensification or rapid improvement in glucose control has been associated with a transitory, reversible ophthalmologic refraction disorder, worsening of diabetic retinopathy, and acute painful peripheral neuropathy. However, long-term glycemic control decreases the risk of diabetic retinopathy and neuropathy.

Weight Gain

Weight gain has occurred with insulin including insulin glargine products and has been attributed to the anabolic effects of insulin and the decrease in glucosuria.

Hypersensitivity Reactions

Local Reactions

Patients taking insulin glargine experienced injection site reactions, including redness, pain, itching, urticaria, edema, and inflammation. In clinical studies in adult patients, there was a higher incidence of injection site pain in insulin glargine-treated patients (2.7%) compared to NPH insulin-treated patients (0.7%). The reports of pain at the injection site did not result in discontinuation of therapy.

Systemic Reactions

Severe, life-threatening, generalized allergy, including anaphylaxis, generalized skin reactions, angioedema, bronchospasm, hypotension, and shock have occurred with insulin, including insulin glargine products and may be life threatening.

6.2 Immunogenicity

As with all therapeutic proteins, there is potential for immunogenicity. The detection of antibody formation is highly dependent on the sensitivity and specificity of the assay. Additionally, the observed incidence of antibody (including neutralizing antibody) positivity in an assay may be influenced by several factors, including assay methodology, sample handling, timing of sample collection, concomitant medications, and underlying disease. For these reasons, comparison of the incidence of antibodies in the studies described below with the incidence of antibodies in other studies or to other insulin glargine products may be misleading.

All insulin products can elicit the formation of insulin antibodies. The presence of such insulin antibodies may increase or decrease the efficacy of insulin and may require adjustment of the insulin dose. In clinical studies of insulin glargine, increases in titers of antibodies to insulin were observed in NPH insulin and insulin glargine treatment groups with similar incidences.

6.3 Postmarketing Experience

The following adverse reactions have been identified during postapproval use of insulin glargine products. Because these reactions are reported voluntarily from a population of uncertain size, it is not always possible to reliably estimate their frequency or establish a causal relationship to drug exposure.

Medication errors have been reported in which rapid-acting insulins and other insulins, have been accidentally administered instead of insulin glargine products.

Localized cutaneous amyloidosis at the injection site has occurred. Hyperglycemia has been reported with repeated insulin injections into areas of localized cutaneous amyloidosis; hypoglycemia has been reported with a sudden change to an unaffected injection site.

7 DRUG INTERACTIONS

Table 8 includes clinically significant drug interactions with Insulin Glargine-yfgn.

Table 8: Clinically Significant Drug Interactions with Insulin Glargine-yfgn
Drugs that May Increase the Risk of Hypoglycemia
Drugs: | Antidiabetic agents, ACE inhibitors, angiotensin II receptor blocking agents, disopyramide, fibrates, fluoxetine, monoamine oxidase inhibitors, pentoxifylline, pramlintide, salicylates, somatostatin analogs (e.g., octreotide), sulfonamide antibiotics, GLP-1 receptor agonists, DPP-4 inhibitors, and SGLT-2 inhibitors.
Intervention: | Dosage reductions and increased frequency of glucose monitoring may be required when Insulin Glargine-yfgn is coadministered with these drugs.
Drugs that May Decrease the Blood Glucose Lowering Effect of Insulin Glargine-yfgn
Drugs: | Atypical antipsychotics (e.g., olanzapine and clozapine), corticosteroids, danazol, diuretics, estrogens, glucagon, isoniazid, niacin, oral contraceptives, phenothiazines, progestogens (e.g., in oral contraceptives), protease inhibitors, somatropin, sympathomimetic agents (e.g., albuterol, epinephrine, terbutaline), and thyroid hormones.
Intervention: | Dosage increases and increased frequency of glucose monitoring may be required when Insulin Glargine-yfgn is coadministered with these drugs.
Drugs that May Increase or Decrease the Blood Glucose Lowering Effect of Insulin Glargine-yfgn
Drugs: | Alcohol, beta-blockers, clonidine, and lithium salts. Pentamidine may cause hypoglycemia, which may sometimes be followed by hyperglycemia.
Intervention: | Dosage adjustment and increased frequency of glucose monitoring may be required when Insulin Glargine-yfgn is coadministered with these drugs.
Drugs that May Blunt Signs and Symptoms of Hypoglycemia
Drugs: | Beta-blockers, clonidine, guanethidine, and reserpine.
Intervention: | Increased frequency of glucose monitoring may be required when Insulin Glargine-yfgn is coadministered with these drugs.

8 USE IN SPECIFIC POPULATIONS

8.1 Pregnancy

Risk Summary

Published studies with use of insulin glargine products during pregnancy have not reported a clear association with insulin glargine products and adverse developmental outcomes (see Data). There are risks to the mother and fetus associated with poorly controlled diabetes in pregnancy (see Clinical Considerations).

Rats and rabbits were exposed to insulin glargine in animal reproduction studies during organogenesis, respectively 50 times and 10 times the human subcutaneous dosage of 0.2 units/kg/day. Overall, the effects of insulin glargine did not generally differ from those observed with regular human insulin (see Data).

In the U.S. general population, the estimated background risk of major birth defects and miscarriage in clinically recognized pregnancies is 2% to 4% and 15% to 20%, respectively. The estimated background risk of major birth defects is 6% to 10% in women with pregestational diabetes with a peri-conceptional HbA1c >7 and has been reported to be as high as 20% to 25% in women with a peri-conceptional HbA1c >10. The estimated background risk of miscarriage for the indicated population is unknown.

Clinical Considerations

Disease-Associated Maternal and/or Embryo-fetal Risk

Hypoglycemia and hyperglycemia occur more frequently during pregnancy in patients with pre-gestational diabetes. Poorly controlled diabetes in pregnancy increases the maternal risk for diabetic ketoacidosis, preeclampsia, spontaneous abortions, preterm delivery, and delivery complications. Poorly controlled diabetes increases the fetal risk for major birth defects, stillbirth, and macrosomia-related morbidity.

Data

Human Data

Published data do not report a clear association with insulin glargine products and major birth defects, miscarriage, or adverse maternal or fetal outcomes when insulin glargine is used during pregnancy. However, these studies cannot definitely establish the absence of any risk because of methodological limitations including small sample size and some lacking comparator groups.

Animal Data

Subcutaneous reproduction and teratology studies have been performed with insulin glargine and regular human insulin in rats and Himalayan rabbits. Insulin glargine was given to female rats before mating, during mating, and throughout pregnancy at doses up to 0.36 mg/kg/day, which is approximately 50 times the recommended human subcutaneous starting dosage of 0.2 units/kg/day (0.007 mg/kg/day), on a mg/kg basis. In rabbits, doses of 0.072 mg/kg/day, which is approximately 10 times the recommended human subcutaneous starting dosage of 0.2 units/kg/day on a mg/kg basis, were administered during organogenesis. The effects of insulin glargine did not generally differ from those observed with regular human insulin in rats or rabbits. However, in rabbits, five fetuses from two litters of the high-dose group exhibited dilation of the cerebral ventricles. Fertility and early embryonic development appeared normal.

8.2 Lactation

Risk Summary

There are either no or only limited data on the presence of insulin glargine products in human milk, the effects on breastfed infant, or the effects on milk production. Endogenous insulin is present in human milk. The developmental and health benefits of breastfeeding should be considered along with the mother's clinical need for Insulin Glargine-yfgn, and any potential adverse effects on the breastfed child from Insulin Glargine-yfgn or from the underlying maternal condition.

8.4 Pediatric Use

The safety and effectiveness of Insulin Glargine-yfgn to improve glycemic control in pediatric patients with diabetes mellitus have been established. Use of Insulin Glargine-yfgn for this indication is supported by Insulin Glargine-yfgn's approval as a biosimilar to insulin glargine and evidence from an adequate and well-controlled study (Study D) in 174 insulin glargine-treated pediatric patients aged 6 to 15 years with type 1 diabetes mellitus and from adequate and well-controlled studies of insulin glargine in adults with diabetes mellitus [see Clinical Pharmacology (12.3), Clinical Studies (14.2)].

In the pediatric clinical study, pediatric patients with type 1 diabetes had a higher incidence of severe symptomatic hypoglycemia compared to the adults in studies with type 1 diabetes [see Adverse Reactions (6.1)].

8.5 Geriatric Use

Of the total number of subjects in controlled clinical studies of patients with type 1 and type 2 diabetes who were treated with insulin glargine, 15% (n=316) were ≥ 65 years of age and 2% (n=42) were ≥ 75 years of age. No overall differences in safety or effectiveness of insulin glargine have been observed between patients 65 years of age and older and younger adult patients.

Nevertheless, caution should be exercised when Insulin Glargine-yfgn is administered to geriatric patients. In geriatric patients with diabetes, the initial dosing, dosage increments, and maintenance dosage should be conservative to avoid hypoglycemic reactions. Hypoglycemia may be difficult to recognize in geriatric patients.

8.6 Renal Impairment

The effect of kidney impairment on the pharmacokinetics of insulin glargine products has not been studied. Some studies with human insulin have shown increased circulating levels of insulin in patients with kidney failure. Frequent glucose monitoring and dosage adjustment may be necessary for Insulin Glargine-yfgn in patients with kidney impairment [see Warnings and Precautions (5.3)].

8.7 Hepatic Impairment

The effect of hepatic impairment on the pharmacokinetics of insulin glargine products has not been studied. Frequent glucose monitoring and dosage adjustment may be necessary for Insulin Glargine-yfgn in patients with hepatic impairment [see Warnings and Precautions (5.3)].

10 OVERDOSAGE

Excess insulin administration may cause hypoglycemia and hypokalemia [see Warnings and Precautions (5.3, 5.6)].

Mild episodes of hypoglycemia can usually be treated with oral carbohydrates. Lowering the insulin dosage, and adjustments in meal patterns or exercise may be needed.

More severe episodes of hypoglycemia with coma, seizure, or neurologic impairment may be treated with glucagon for emergency use or concentrated intravenous glucose. After apparent clinical recovery from hypoglycemia, continued observation and additional carbohydrate intake may be necessary to avoid recurrence of hypoglycemia.

Hypokalemia must be corrected appropriately.

11 DESCRIPTION

Insulin glargine-yfgn is a long-acting human insulin analog produced by recombinant DNA technology utilizing a recombinant yeast strain, Pichia pastoris. Insulin glargine-yfgn differs from human insulin in that the amino acid asparagine at position A21 is replaced by glycine and two arginines are added to the C-terminus of the B-chain. Insulin glargine-yfgn has a molecular weight of 6063 Da.

Insulin Glargine-yfgn is a sterile, clear and colorless solution for subcutaneous use in a 10 mL multiple-dose vial and a 3 mL single-patient-use prefilled pen.

Prefilled Pen and Vial: Each mL contains 100 units of insulin glargine-yfgn and the inactive ingredients: glycerol (20 mg), metacresol (2.7 mg), zinc chloride (content adjusted to provide 30 mcg zinc ion), and Water for Injection, USP. The vial also contains polysorbate 20 (20 mcg). The pH is adjusted by addition of aqueous solutions of hydrochloric acid and/or sodium hydroxide. Insulin Glargine-yfgn has a pH of approximately 4.

12 CLINICAL PHARMACOLOGY

12.1 Mechanism of Action

The primary activity of insulin, including insulin glargine products, is regulation of glucose metabolism. Insulin and its analogs lower blood glucose by stimulating peripheral glucose uptake, especially by skeletal muscle and fat, and by inhibiting hepatic glucose production. Insulin inhibits lipolysis and proteolysis, and enhances protein synthesis.

12.2 Pharmacodynamics

In clinical studies, the glucose-lowering effect on a molar basis (i.e., when given at the same doses) of intravenous insulin glargine is approximately the same as that for human insulin. Figure 1 shows results from a study in patients with type 1 diabetes conducted for a maximum of 24 hours after subcutaneous injection of insulin glargine or NPH insulin. The median time between subcutaneous injection and the end of pharmacological effect was 14.5 hours (range: 9.5 to 19.3 hours) for NPH insulin, and 24 hours (range: 10.8 to > 24 hours) (24 hours was the end of the observation period) for insulin glargine.

Figure 1: Glucose-Lowering Effect Over 24 Hours in Patients with Type 1 Diabetes

* Determined as amount of glucose infused to maintain constant plasma glucose levels

The duration of action after abdominal, deltoid, or thigh subcutaneous administration of insulin glargine was similar. The time course of action of insulins, including insulin glargine products, may vary between patients and within the same patient.

12.3 Pharmacokinetics

Absorption

After subcutaneous injection of insulin glargine in healthy subjects and in patients with diabetes, the insulin serum concentrations indicated a slower, more prolonged absorption and a relatively constant concentration/time profile over 24 hours with no pronounced peak in comparison to NPH insulin.

Elimination

Metabolism
A metabolism study in humans indicates that insulin glargine is partly metabolized at the carboxyl terminus of the B chain in the subcutaneous depot to form two active metabolites with in vitro activity similar to that of human insulin, M1 (21A-Gly-insulin) and M2 (21A-Gly-des- 30B-Thr-insulin). Unchanged drug and these degradation products are also present in the circulation.

Specific Populations

Age, Race, Body Mass Index, and Gender

Effect of age, race, body mass index (BMI), and gender on the pharmacokinetics of insulin glargine products has not been evaluated. However, in controlled clinical studies in adults (n = 3,890) and a controlled clinical study in pediatric patients (n = 349), subgroup analyses based on age, race, BMI, and gender did not show differences in safety and efficacy between insulin glargine and NPH insulin [see Clinical Studies (14)].

13 NONCLINICAL TOXICOLOGY

13.1 Carcinogenesis, Mutagenesis, Impairment of Fertility

In mice and rats, standard two-year carcinogenicity studies with insulin glargine were performed at doses up to 0.455 mg/kg, which was for the rat approximately 65 times the recommended human subcutaneous starting dosage of 0.2 units/kg/day (0.007 mg/kg/day) on a mg/kg basis. Histiocytomas were found at injection sites in male rats and mice in acid vehicle containing groups and are considered a response to chronic tissue irritation and inflammation in rodents. These tumors were not found in female animals, in saline control, or insulin comparator groups using a different vehicle.

Insulin glargine was not mutagenic in tests for detection of gene mutations in bacteria and mammalian cells (Ames and HGPRT-test) and in tests for detection of chromosomal aberrations (cytogenetics in vitro in V79 cells and in vivo in Chinese hamsters).

In a combined fertility and prenatal and postnatal study in male and female rats at subcutaneous doses up to 0.36 mg/kg/day, which was approximately 50 times the recommended human subcutaneous starting dosage of 0.2 units/kg/day (0.007 mg/kg/day) maternal toxicity due to dose-dependent hypoglycemia, including some deaths, was observed. Consequently, a reduction of the rearing rate occurred in the high-dose group only. Similar effects were observed with NPH insulin.

14 CLINICAL STUDIES

14.1 Overview of Clinical Studies

The safety and effectiveness of insulin glargine given once-daily at bedtime was compared to that of once-daily and twice-daily NPH insulin in open-label, randomized, active-controlled, parallel studies of 2,327 adult patients and 349 pediatric patients with type 1 diabetes mellitus and 1,563 adult patients with type 2 diabetes mellitus (see Tables 9-11). In general, the reduction in glycated hemoglobin (HbA1c) with insulin glargine was similar to that with NPH insulin.

14.2 Clinical Studies in Adult and Pediatric Patients with Type 1 Diabetes

Adult Patients with Type 1 Diabetes
In two clinical studies (Studies A and B), adult patients with type 1 diabetes (Study A, n = 585, Study B n = 534) were randomized to 28 weeks of basal-bolus treatment with insulin glargine or NPH insulin. Regular human insulin was administered before each meal. Insulin glargine was administered at bedtime. NPH insulin was administered either as once daily at bedtime or in the morning and at bedtime when used twice daily.

In Study A, the average age was 39 years. The majority of patients were White (99%) and 56% were male. The mean BMI was approximately 24.9 kg/m^2. The mean duration of diabetes was 16 years.

In Study B, the average age was 39 years. The majority of patients were White (95%) and 51% were male. The mean BMI was approximately 25.8 kg/m^2. The mean duration of diabetes was 17 years.

In another clinical study (Study C), patients with type 1 diabetes (n = 619) were randomized to 16 weeks of basal-bolus treatment with insulin glargine or NPH insulin. Insulin lispro was used before each meal. Insulin glargine was administered once daily at bedtime and NPH insulin was administered once or twice daily. The average age was 39 years. The majority of patients were White (97%) and 51% were male. The mean BMI was approximately 25.6 kg/m^2. The mean duration of diabetes was 19 years.

In these 3 adult studies, insulin glargine and NPH insulin had similar effects on HbA1c (Table 9) with a similar overall rate of severe symptomatic hypoglycemia [see Adverse Reactions (6.1)].

Table 9: Type 1 Diabetes Mellitus – Adults
Treatment duration; Treatment in combination with | Study A; 28 weeks; Regular insulin |  | Study B; 28 weeks; Regular insulin |  | Study C; 16 weeks; Insulin lispro
Treatment duration; Treatment in combination with | Insulin Glargine | NPH | Insulin Glargine | NPH | Insulin Glargine | NPH
Number of subjects treated | 292 | 293 | 264 | 270 | 310 | 309
HbA1c
Baseline HbA1c | 8.0 | 8.0 | 7.7 | 7.7 | 7.6 | 7.7
Adjusted mean change at study end | +0.2 | +0.1 | -0.2 | -0.2 | -0.1 | -0.1
Treatment Difference (95% CI) | +0.1 (0.0; +0.2) |  | +0.1 (-0.1; +0.2) |  | 0.0 (-0.1; +0.1)
Basal insulin dose
Baseline mean | 21 | 23 | 29 | 29 | 28 | 28
Mean change from baseline | -2 | 0 | -4 | +2 | -5 | +1
Total insulin dose
Baseline mean | 48 | 52 | 50 | 51 | 50 | 50
Mean change from baseline | -1 | 0 | 0 | +4 | -3 | 0
Fasting blood glucose (mg/dL)
Baseline mean | 167 | 166 | 166 | 175 | 175 | 173
Adj. mean change from baseline | -21 | -16 | -20 | -17 | -29 | -12
Body weight (kg)
Baseline mean | 73.2 | 74.8 | 75.5 | 75.0 | 74.8 | 75.6
Mean change from baseline | 0.1 | -0.0 | 0.7 | 1.0 | 0.1 | 0.5

Pediatric Patients with Type 1 Diabetes

In a randomized, controlled clinical study (Study D), pediatric patients (age range 6 to 15 years) with type 1 diabetes (n = 349) were treated for 28 weeks with a basal-bolus insulin regimen where regular human insulin was used before each meal. Insulin glargine was administered once daily at bedtime and NPH insulin was administered once or twice daily. The average age was 11.7 years. The majority of patients were White (97%) and 52% were male. The mean BMI was approximately 18.9 kg/m^2. The mean duration of diabetes was 5 years. Similar effects on HbA1c (Table 10) were observed in both treatment groups [see Adverse Reactions (6.1)].

Table 10: Type 1 Diabetes Mellitus – Pediatric Patients
Treatment duration; Treatment in combination with | Study D; 28 weeks; Regular insulin
 | Insulin Glargine + Regular insulin | NPH+; Regular insulin
Number of subjects treated | 174 | 175
HbA1c
Baseline mean | 8.5 | 8.8
Change from baseline (adjusted mean) | +0.3 | +0.3
Difference from NPH (adjusted mean) | 0.0
(95% CI) | (-0.2; +0.3)
Basal insulin dose
Baseline mean | 19 | 19
Mean change from baseline | -1 | +2
Total insulin dose
Baseline mean | 43 | 43
Mean change from baseline | +2 | +3
Fasting blood glucose (mg/dL)
Baseline mean | 194 | 191
Mean change from baseline | -23 | -12
Body weight (kg)
Baseline mean | 45.5 | 44.6
Mean change from baseline | 2.2 | 2.5

14.3 Clinical Studies in Adults with Type 2 Diabetes

In a randomized, controlled clinical study (Study E) in 570 adults with type 2 diabetes, insulin glargine was evaluated for 52 weeks in combination with oral antidiabetic medications (a sulfonylurea, metformin, acarbose, or combinations of these drugs). The average age was 60 years old. The majority of patients were White (93%) and 54% were male. The mean BMI was approximately 29.1 kg/m^2. The mean duration of diabetes was 10 years. Insulin glargine administered once daily at bedtime was as effective as NPH insulin administered once daily at bedtime in reducing HbA1c and fasting glucose (Table 11). The rate of severe symptomatic hypoglycemia was similar in insulin glargine and NPH insulin treated patients [see Adverse Reactions (6.1)].

In a randomized, controlled clinical study (Study F), in adult patients with type 2 diabetes not using oral antidiabetic medications (n = 518), a basal-bolus regimen of insulin glargine once daily at bedtime or NPH insulin administered once or twice daily was evaluated for 28 weeks. Regular human insulin was used before meals, as needed. The average age was 59 years. The majority of patients were White (81%) and 60% were male. The mean BMI was approximately 30.5 kg/m^2. The mean duration of diabetes was 14 years. Insulin glargine had similar effectiveness as either once- or twice-daily NPH insulin in reducing HbA1c and fasting glucose (Table 11) with a similar incidence of hypoglycemia [see Adverse Reactions (6.1)].

In a randomized, controlled clinical study (Study G), adult patients with type 2 diabetes were randomized to 5 years of treatment with once-daily insulin glargine or twice-daily NPH insulin. For patients not previously treated with insulin, the starting dosage of insulin glargine or NPH insulin was 10 units daily. Patients who were already treated with NPH insulin either continued on the same total daily NPH insulin dose or started insulin glargine at a dosage that was 80% of the total previous NPH insulin dosage. The primary endpoint for this study was a comparison of the progression of diabetic retinopathy by 3 or more steps on the Early Treatment Diabetic Retinopathy Study (ETDRS) scale. HbA1c change from baseline was a secondary endpoint. Similar glycemic control in the 2 treatment groups was desired in order to not confound the interpretation of the retinal data. Patients or study personnel used an algorithm to adjust the insulin glargine and NPH insulin dosages to a target fasting plasma glucose ≤ 100 mg/dL. After the insulin glargine or NPH insulin dosage was adjusted, other anti-diabetic agents, including premeal insulin were to be adjusted or added. The average age was 55 years. The majority of patients were White (85%) and 54% were male. The mean BMI was approximately 34.3 kg/m^2. The mean duration of diabetes was 11 years. The insulin glargine group had a smaller mean reduction from baseline in HbA1c compared to the NPH insulin group, which may be explained by the lower daily basal insulin doses in the insulin glargine group (Table 11). The incidences of severe symptomatic hypoglycemia were similar between groups [see Adverse Reactions (6.1)].

Table 11: Type 2 Diabetes Mellitus – Adults
Treatment duration; Treatment in combination with | Study E; 52 weeks; Oral agents |  | Study F; 28 weeks; Regular insulin |  | Study G; 5 years; Regular insulin
Treatment duration; Treatment in combination with | Insulin Glargine | NPH | Insulin Glargine | NPH | Insulin Glargine | NPH
Number of subjects treated | 289 | 281 | 259 | 259 | 513 | 504
HbA1c
Baseline mean | 9.0 | 8.9 | 8.6 | 8.5 | 8.4 | 8.3
Adjusted mean change from baseline | -0.5 | -0.4 | -0.4 | -0.6 | -0.6 | -0.8
Insulin Glargine ‒ NPH | -0.1 |  | +0.2 |  | +0.2
95% CI for Treatment difference | (-0.3; +0.1) |  | (0.0; +0.4) |  | (+0.1; +0.4)
Basal insulin dose [In Study G, the baseline dose of basal or total insulin was the first available on-treatment dose prescribed during the study (on visit month 1.5).]
Baseline mean | 14 | 15 | 44.1 | 45.5 | 39 | 44
Mean change from baseline | +12 | +9 | -1 | +7 | +23 | +30
Total insulin dose
Baseline mean | 14 | 15 | 64 | 67 | 48 | 53
Mean change from baseline | +12 | +9 | +10 | +13 | +41 | +40
Fasting blood glucose (mg/dL)
Baseline mean | 179 | 180 | 164 | 166 | 190 | 180
Adj. mean change from baseline | -49 | -46 | -24 | -22 | -45 | -44
Body weight (kg)
Baseline mean | 83.5 | 82.1 | 89.6 | 90.7 | 100 | 99
Adj. mean change from baseline | 2.0 | 1.9 | 0.4 | 1.4 | 3.7 | 4.8

14.4 Additional Clinical Studies in Adults with Diabetes Type 1 and Type 2

Different Timing of Insulin Glargine Administration in Diabetes Type 1 and Diabetes Type 2
The safety and efficacy of once daily insulin glargine administered either at pre-breakfast, pre-dinner, or at bedtime were evaluated in a randomized, controlled clinical study in adult patients with type 1 diabetes (Study H, n = 378). Patients were also treated with insulin lispro at mealtime. The average age was 41 years. All patients were White (100%) and 54% were male. The mean BMI was approximately 25.3 kg/m^2. The mean duration of diabetes was 17 years.

Insulin glargine administered at pre-breakfast or at pre-dinner (both once daily) resulted in similar reductions in HbA1c compared to that with bedtime administration (see Table 12). In these patients, data are available from 8-point home glucose monitoring. The maximum mean blood glucose was observed just prior to insulin glargine injection regardless of time of administration. In this study, 5% of patients in the insulin glargine-breakfast group discontinued treatment because of lack of efficacy. No patients in the other two groups (pre-dinner, bedtime) discontinued for this reason.

The safety and efficacy of once daily insulin glargine administered pre-breakfast or at bedtime were also evaluated in a randomized, active-controlled clinical study (Study I, n = 697) in patients with type 2 diabetes not adequately controlled on oral antidiabetic therapy. All patients in this study also received glimepiride 3 mg daily. The average age was 61 years. The majority of patients were White (97%) and 54% were male. The mean BMI was approximately 28.7 kg/m^2. The mean duration of diabetes was 10 years. Insulin glargine given before breakfast was at least as effective in lowering HbA1c as insulin glargine given at bedtime or NPH insulin given at bedtime (see Table 12).

Table 12: Study of Different Times of Once Daily Insulin Glargine Dosing in Type 1 (Study H) and Type 2 (Study I) Diabetes Mellitus

Treatment duration Treatment in combination with | Study H 24 weeks Insulin lispro |  |  | Study I 24 weeks Glimepiride
Treatment duration Treatment in combination with | Insulin Glargine Before Breakfast | Insulin Glargine Before Dinner | Insulin Glargine Bedtime | Insulin Glargine Before Breakfast | Insulin Glargine Bedtime | NPH Bedtime
Number of subjects treated [Intent-to-treat] | 112 | 124 | 128 | 234 | 226 | 227
HbA1c
Baseline mean | 7.6 | 7.5 | 7.6 | 9.1 | 9.1 | 9.1
Mean change from baseline | -0.2 | -0.1 | 0.0 | -1.3 | -1.0 | -0.8
Basal insulin dose (Units)
Baseline mean | 22 | 23 | 21 | 19 | 20 | 19
Mean change from baseline | 5 | 2 | 2 | 11 | 18 | 18
Total insulin dose (Units) | - | - | - | NA† | NA† | NA†
Baseline mean | 52 | 52 | 49 | - | - | -
Mean change from baseline | 2 | 3 | 2 | - | - | -
Body weight (kg)
Baseline mean | 77.1 | 77.8 | 74.5 | 80.7 | 82 | 81
Mean change from baseline | 0.7 | 0.1 | 0.4 | 3.9 | 3.7 | 2.9

† Not applicable

Progression of Retinopathy Evaluation in Adults with Diabetes Type 1 and Diabetes Type 2

Insulin glargine was compared to NPH insulin in a 5-year randomized clinical study that evaluated the progression of retinopathy as assessed with fundus photography using a grading protocol derived from the Early Treatment Diabetic Retinopathy Scale (ETDRS). Patients had type 2 diabetes (mean age 55 years) with no (86%) or mild (14%) retinopathy at baseline. Mean baseline HbA1c was 8.4%. The primary outcome was progression by 3 or more steps on the ETDRS scale at study endpoint. Patients with prespecified postbaseline eye procedures (pan-retinal photocoagulation for proliferative or severe nonproliferative diabetic retinopathy, local photocoagulation for new vessels, and vitrectomy for diabetic retinopathy) were also considered as 3-step progressors regardless of actual change in ETDRS score from baseline. Retinopathy graders were blinded to treatment group assignment.

The results for the primary endpoint are shown in Table 13 for both the per-protocol and intent-to-treat populations and indicate similarity of insulin glargine to NPH in the progression of diabetic retinopathy as assessed by this outcome. In this study, the numbers of retinal adverse events reported for insulin glargine and NPH insulin treatment groups were similar for adult patients with type 1 and type 2 diabetes.

Table 13: Number (%) of Patients with 3 or More Step Progression on ETDRS Scale at Endpoint
 | Insulin Glargine (%) | NPH (%) | Difference [Difference = Insulin Glargine – NPH] , [Using a generalized linear model (SAS GENMOD) with treatment and baseline HbA1c strata (cutoff 9.0%) as the classified independent variables, and with binomial distribution and identity link function] (SE) | 95% CI for difference
Per-protocol | 53/374 (14.2%) | 57/363 (15.7%) | -2.0% (2.6%) | -7.0% to +3.1%
Intent-to-Treat | 63/502 (12.5%) | 71/487 (14.6%) | -2.1% (2.1%) | -6.3% to +2.1%

The ORIGIN Study of Major Cardiovascular Outcomes in Patients with Established CV Disease or CV Risk Factors

The Outcome Reduction with Initial Glargine Intervention study (i.e., ORIGIN) was an open-label, randomized, 2-by-2, factorial design study. One intervention in ORIGIN compared the effect of insulin glargine to standard care on major adverse cardiovascular (CV) outcomes in 12,537 adults ≥ 50 years of age with:

- Abnormal glucose levels (i.e., impaired fasting glucose [IFG] and/or impaired glucose tolerance [IGT]) or early type 2 diabetes mellitus and
- Established CV disease or CV risk factors at baseline.

The objective of the study was to demonstrate that insulin glargine use could significantly lower the risk of major CV outcomes compared to standard care. There were two coprimary composite CV endpoints:

- The first coprimary endpoint was the time to first occurrence of a major adverse CV event defined as the composite of CV death, nonfatal myocardial infarction, and nonfatal stroke.
- The second coprimary endpoint was the time to the first occurrence of CV death or nonfatal myocardial infarction or nonfatal stroke or revascularization procedure or hospitalization for heart failure.

Patients were randomized to either insulin glargine (N = 6,264) titrated to a goal fasting plasma glucose of ≤ 95 mg/dL or to standard care (N = 6,273). Anthropometric and disease characteristics were balanced at baseline. The mean age was 64 years and 8% of patients were 75 years of age or older. The majority of patients were male (65%). Fifty nine percent were White, 25% were Latin, 10% were Asian and 3% were Black or African American. The median baseline BMI was 29 kg/m^2. Approximately 12% of patients had abnormal glucose levels (IGT and/or IFG) at baseline and 88% had type 2 diabetes. For patients with type 2 diabetes, 59% were treated with a single oral antidiabetic drug, 23% had known diabetes but were on no antidiabetic drug and 6% were newly diagnosed during the screening procedure. The mean HbA1c (SD) at baseline was 6.5% (1.0). Fifty-nine percent of the patients had a prior CV event and 39% had documented coronary artery disease or other CV risk factors.

Vital status was available for 99.9% and 99.8% of patients randomized to insulin glargine and standard care respectively at end of study. The median duration of follow-up was 6.2 years (range: 8 days to 7.9 years). The mean HbA1c (SD) at the end of the study was 6.5% (1.1) and 6.8% (1.2) in the insulin glargine and standard care group respectively. The median dose of insulin glargine at end of study was 0.45 U/kg. Eighty-one percent of patients randomized to insulin glargine were using insulin glargine at end of the study. The mean change in body weight from baseline to the last treatment visit was 2.2 kg greater in the insulin glargine group than in the standard care group.

Overall, the incidence of major adverse CV outcomes was similar between groups (see Table 14). All-cause mortality was also similar between groups.

Table 14: Cardiovascular Outcomes in ORIGIN in Patients with Established CV Disease or CV Risk Factors – Time to First Event Analyses
 | Insulin Glargine N = 6,264 | Standard Care; N = 6,273 | Insulin Glargine vs Standard Care
 | n; (Events per 100 PY) | n; (Events per 100 PY) | Hazard Ratio (95% CI)
Coprimary endpoints
CV death, nonfatal myocardial infarction, or nonfatal stroke | 1041; (2.9) | 1013; (2.9) | 1.02 (0.94, 1.11)
CV death, nonfatal myocardial infarction, nonfatal stroke, hospitalization for heart failure or revascularization procedure | 1792; (5.5) | 1727; (5.3) | 1.04 (0.97, 1.11)
Components of coprimary endpoints
CV death | 580 | 576 | 1.00 (0.89, 1.13)
Myocardial Infarction (fatal or nonfatal) | 336 | 326 | 1.03 (0.88, 1.19)
Stroke (fatal or nonfatal) | 331 | 319 | 1.03 (0.89, 1.21)
Revascularizations | 908 | 860 | 1.06 (0.96, 1.16)
Hospitalization for heart failure | 310 | 343 | 0.90 (0.77, 1.05)

In the ORIGIN study, the overall incidence of cancer (all types combined) or death from cancer (Table 15) was similar between treatment groups.

Table 15: Cancer Outcomes in ORIGIN – Time to First Event Analyses
 | Insulin Glargine N = 6,264 | Standard Care; N = 6,273 | Insulin Glargine vs Standard Care
 | n; (Events per 100 PY) | n; (Events per 100 PY) | Hazard Ratio (95% CI)
Cancer endpoints
Any cancer event (new or recurrent) | 559; (1.56) | 561; (1.56) | 0.99 (0.88, 1.11)
New cancer events | 524; (1.46) | 535; (1.49) | 0.96 (0.85, 1.09)
Death due to Cancer | 189; (0.51) | 201; (0.54) | 0.94 (0.77, 1.15)

16 HOW SUPPLIED/STORAGE AND HANDLING

16.1 How Supplied

Insulin Glargine-yfgn injection is supplied as a clear and colorless solution containing 100 units/mL (U-100) available as follows:

Insulin Glargine-yfgn | NDC Number | Package Size
3 mL single-patient-use prefilled pen | 72572-422-01 | 1 pen per carton
3 mL single-patient-use prefilled pen | 72572-422-05 | 5 pens per carton

Additional Information about Insulin Glargine-yfgn:

- The Insulin Glargine-yfgn prefilled pen dials in 1-unit increments.
- Needles are not included in the packs.

Embecta Ultra-Fine needles are compatible with this pen.

16.2 Storage

Dispense in the original sealed carton with the enclosed Instructions for Use.

Store unused Insulin Glargine-yfgn in a refrigerator between 2° to 8°C (36° to 46°F). Do not freeze. Discard Insulin Glargine-yfgn if it has been frozen. Protect Insulin Glargine-yfgn from direct heat and light.

Storage conditions are summarized in the following table:

 | Not in-use (unopened); Refrigerated; (2° to 8°C [36° to 46°F]) | Not in-use (unopened); Room Temperature; (up to 30°C [86°F]) | In-use; (opened); (see temperature below)
3 mL single-patient-use prefilled pen | Until expiration date | 28 days | 28 days; Room temperature only; (Do not refrigerate)

17 PATIENT COUNSELING INFORMATION

Advise the patient to read the FDA-approved patient labeling (Patient Information and Instructions for Use). There are separate Instructions for Use for the vial and prefilled pen.

Never Share an Insulin Glargine-yfgn Prefilled Pen or Insulin Syringe Between Patients

Advise patients that they must never share a Insulin Glargine-yfgn prefilled pen with another person, even if the needle is changed. Advise patients using Insulin Glargine-yfgn vials not to re-use or share needles or insulin syringes with another person. Sharing carries a risk for transmission of blood-borne pathogens [see Warnings and Precautions (5.1)].

Hyperglycemia or Hypoglycemia

Inform patients that hypoglycemia is the most common adverse reaction with insulin. Inform patients of the symptoms of hypoglycemia (e.g., impaired ability to concentrate and react). This may present a risk in situations where these abilities are especially important, such as driving or operating other machinery. Advise patients who have frequent hypoglycemia or reduced or absent warning signs of hypoglycemia to use caution when driving or operating machinery [see Warnings and Precautions (5.3)].

Advise patients that changes in insulin regimen can predispose to hyperglycemia or hypoglycemia and that changes in insulin regimen should be made under close medical supervision [see Warnings and Precautions (5.2)].

Hypoglycemia Due to Medication Errors

Instruct patients to always check the insulin label before each injection to reduce the risk of a medication error [see Warnings and Precautions (5.4)].

Hypersensitivity Reactions

Advise patients that hypersensitivity reactions have occurred with insulin glargine products. Inform patients about the symptoms of hypersensitivity reactions [see Warnings and Precautions (5.5)].

LANTUS is a registered trademark of Sanofi-Aventis Deutschland gmbh.

Distributed by:

Civica, Inc.

Lehi, Utah 84048

Manufactured by:
Biocon Biologics Inc.
245 Main St, 2nd Floor
Cambridge, MA 02142 U.S.A
U.S. License No. 2324
Product of Malaysia

PATIENT INFORMATION

Insulin Glargine-yfgn (in´ su lin glar´ jeen)

injection, for subcutaneous use

100 units/mL (U-100)

This product is insulin glargine-yfgn.

Do not share your Insulin Glargine-yfgn pen with other people, even if the needle has been changed. You may give other people a serious infection, or get a serious infection from them.

What is Insulin Glargine-yfgn?

Insulin Glargine-yfgn is a long-acting man-made insulin used to control high blood sugar in adults and children with diabetes mellitus. Insulin Glargine-yfgn is not for use to treat diabetic ketoacidosis.

Who should not use Insulin Glargine-yfgn?

Do not use Insulin Glargine-yfgn if you:

- are having an episode of low blood sugar (hypoglycemia).
- have an allergy to insulin glargine products or any of the ingredients in Insulin Glargine-yfgn. See the end of this Patient Information leaflet for a complete list of ingredients in Insulin Glargine-yfgn.

What should I tell my healthcare provider before using Insulin Glargine-yfgn?

Before using Insulin Glargine-yfgn, tell your healthcare provider about all your medical conditions including if you:

- have liver or kidney problems.
- take other medicines, especially ones called TZDs (thiazolidinediones).
- have heart failure or other heart problems. If you have heart failure, it may get worse while you take TZDs with Insulin Glargine-yfgn.
- are pregnant, planning to become pregnant, or are breastfeeding. It is not known if Insulin Glargine-yfgn may harm your unborn baby or breastfeeding baby.

Tell your healthcare provider about all the medicines you take including prescription and over-the-counter medicines, vitamins, and herbal supplements.

Before you start using Insulin Glargine-yfgn, talk to your healthcare provider about low blood sugar and how to manage it.

How should I use Insulin Glargine-yfgn?

- Read the detailed Instructions for Use that come with your Insulin Glargine-yfgn single-patient use prefilled pen.
- Use Insulin Glargine-yfgn exactly as your healthcare provider tells you to. Your healthcare provider should tell you how much Insulin Glargine-yfgn to use and when to use it.
- Know the amount of Insulin Glargine-yfgn you use. Do not change the amount of Insulin Glargine-yfgn you use unless your healthcare provider tells you to.
- Check your insulin label each time you give your injection to make sure you are using the correct insulin.
- The dose counter on your pen shows your dose of Insulin Glargine-yfgn. Do not make any dose changes unless your healthcare provider tells you to.
- Do not use a syringe to remove Insulin Glargine-yfgn from your disposable prefilled pen.
- Do not re-use needles. Always use a new needle for each injection. Re-use of needles increases your risk of having blocked needles, which may cause you to get the wrong dose of Insulin Glargine-yfgn. Using a new needle for each injection lowers your risk of getting an infection. If your needle is blocked, follow the instructions in Step 3 of the Instructions for Use.
- You may take Insulin Glargine-yfgn at any time during the day but you must take it at the same time every day.
- Insulin Glargine-yfgn is injected under the skin (subcutaneously) of your upper legs (thighs), upper arms, or stomach area (abdomen).
- Do not use Insulin Glargine-yfgn in an insulin pump or inject Insulin Glargine-yfgn into your vein (intravenously).
- Change (rotate) your injection sites within area you chose with each dose to reduce your risk of getting lipodystrophy (pits in skin or thickened skin) and localized cutaneous amyloidosis (skin with lumps) at the injection sites.
  - Do not use the exact same spot for each injection.
  - Do not inject where the skin has pits, is thickened, or has lumps.
  - Do not inject where skin is tender, bruised, scaly or hard, or into scars or damaged skin.
- Do not mix Insulin Glargine-yfgn with any other type of insulin or liquid medicine.
- Check your blood sugar levels. Ask your healthcare provider what your blood sugar should be and when you should check your blood sugar levels.

Keep Insulin Glargine-yfgn and all medicines out of the reach of children.

Your dose of Insulin Glargine-yfgn may need to change because of:

- a change in level of physical activity or exercise, weight gain or loss, increased stress, illness, change in diet, or because of the medicines you take.

What should I avoid while using Insulin Glargine-yfgn?

While using Insulin Glargine-yfgn do not:

- drive or operate heavy machinery, until you know how Insulin Glargine-yfgn affects you.
- drink alcohol or use over-the-counter medicines that contain alcohol.

What are the possible side effects of Insulin Glargine-yfgn and other insulins?

Insulin Glargine-yfgn may cause serious side effects that can lead to death, including:

- low blood sugar (hypoglycemia). Signs and symptoms that may indicate low blood sugar include:
  - dizziness or light-headedness, sweating, confusion, headache, blurred vision, slurred speech, shakiness, fast heartbeat, anxiety, irritability or mood change, hunger.
- severe allergic reaction (whole body reaction). Get medical help right away if you have any of these signs or symptoms of a severe allergic reaction:
  - a rash over your whole body, trouble breathing, a fast heartbeat, or sweating.
- low potassium in your blood (hypokalemia).
- heart failure. Taking certain diabetes pills called TZDs (thiazolidinediones) with Insulin Glargine-yfgn may cause heart failure in some people. This can happen even if you have never had heart failure or heart problems before. If you already have heart failure it may get worse while you take TZDs with Insulin Glargine-yfgn. Your healthcare provider should monitor you closely while you are taking TZDs with Insulin Glargine-yfgn. Tell your healthcare provider if you have any new or worse symptoms of heart failure including:
  - shortness of breath, swelling of your ankles or feet, sudden weight gain.

Treatment with TZDs and Insulin Glargine-yfgn may need to be changed or stopped by your healthcare provider if you have new or worse heart failure.

Get emergency medical help if you have:

- trouble breathing; shortness of breath; fast heartbeat; swelling of your face, tongue, or throat; sweating; extreme drowsiness; dizziness; confusion.

The most common side effects of Insulin Glargine-yfgn include:

- low blood sugar (hypoglycemia); weight gain; allergic reactions, including reactions at your injection site; skin thickening or pits at the injection site (lipodystrophy).

These are not all the possible side effects of Insulin Glargine-yfgn. Call your doctor for medical advice about side effects. You may report side effects to FDA at 1-800-FDA-1088.

General information about the safe and effective use of Insulin Glargine-yfgn.

Medicines are sometimes prescribed for purposes other than those listed in a Patient Information leaflet. Do not use Insulin Glargine-yfgn for a condition for which it was not prescribed. Do not give Insulin Glargine-yfgn to other people, even if they have the same symptoms that you have. It may harm them.

This Patient Information leaflet summarizes the most important information about Insulin Glargine-yfgn. If you would like more information, talk with your healthcare provider. You can ask your healthcare provider or pharmacist for information about Insulin Glargine-yfgn that is written for healthcare professionals.

What are the ingredients in Insulin Glargine-yfgn?

- Active ingredient: insulin glargine-yfgn
- 3 mL prefilled pen inactive ingredients: glycerol, metacresol, zinc chloride and Water for Injection. Hydrochloric acid and sodium hydroxide may be added to adjust the pH.

For more information, call Biocon Biologics at 1-833-986-1468
Manufactured by:

Biocon Biologics Inc.
245 Main St, 2nd Floor

Cambridge, MA 02142 U.S.A.
U.S. License No. 2324
Product of Malaysia

This Patient Information has been approved by the U.S. Food and Drug Administration.

Revised: 07/2025

Distributed by:

Civica, Inc.

Lehi, Utah 84048

Manufactured by:

Biocon Biologics Inc.

245 Main St, 2nd Floor

Cambridge, MA 02142 U.S.A

U.S. License No. 2324

Product of Malaysia

INSTRUCTIONS FOR USE

Insulin Glargine-yfgn (in' su lin glar' jeen)

injection, for subcutaneous use

3 mL Single-Patient-Use PREFILLED PEN: 100 units/mL (U-100)

This product is insulin glargine-yfgn.

Read these Instructions for Use before you start using the Insulin Glargine-yfgn pen and each time you get a new Insulin Glargine-yfgn pen. There may be new information. This information does not take the place of talking to your healthcare provider about your medical condition or your treatment.

Do not share your Insulin Glargine-yfgn pen with other people, even if the needle has been changed. You may give other people a serious infection, or get a serious infection from them.

People who are blind or have vision problems should not use the Insulin Glargine-yfgn prefilled pen without help from a person trained to use the Insulin Glargine-yfgn prefilled pen.

Insulin Glargine-yfgn is a disposable prefilled pen used to inject Insulin Glargine-yfgn. Each Insulin Glargine-yfgn pen has 300 units of insulin which can be used for multiple injections. You can select doses from 1 to 80 units in steps of 1 unit. The pen plunger moves with each dose. The plunger will only move to the end of the cartridge when 300 units of Insulin Glargine-yfgn have been given.

Important Information You Need to Know Before Injecting Insulin Glargine-yfgn:

- Do not use your pen if it is damaged or if you are not sure that it is working properly.
- Do not use a syringe to remove Insulin Glargine-yfgn from your pen.
- Do not reuse needles. If you do, you might get the wrong dose of Insulin Glargine-yfgn or you may increase the chances of getting an infection.
- Always perform a safety test (see Step 3).
- Always carry a spare pen and spare needles in case they get lost or stop working.
- Change (rotate) your injection sites within the area you choose for each dose (see "Places to Inject").

Learn to Inject

- Talk with your healthcare provider about how to inject before using your pen.
- Ask for help if you have problems handling the pen, for example if you have problems with your sight.
- Read all these instructions before using your pen. If you do not follow all these instructions, you may get too much or too little insulin.

Need Help?

If you have any questions about your pen or about diabetes, ask your healthcare provider, or call Biocon Biologics at 1-833-986-1468

Extra Items You Will Need

- A new sterile needle (see Step 2).
- An alcohol swab.
- A puncture-resistant container for used needles and pens. (See "Throwing your pen away")

Places to inject

- Inject your insulin exactly as your healthcare provider has shown you.
- Inject your insulin under the skin (subcutaneously) of your upper legs (thighs), upper arms, or stomach area (abdomen).
- Change (rotate) your injection sites within the area you choose for each dose to reduce your risk of getting lipodystrophy (pits in skin or thickened skin) and localized cutaneous amyloidosis (skin with lumps) at the injection sites.
- Do not inject where the skin has pits, is thickened, or has lumps.
- Do not inject where the skin is tender, bruised, scaly or hard, or into scars or damaged skin.

Get to know your pen

Step 1: Check your pen

Take a new pen out of the refrigerator at least 1 hour before you inject. Cold insulin is more painful to inject.

1A Check the name and expiration date on the label of your pen.

- Make sure you have the correct insulin (See Figure a).

- Do not use your pen after the expiration date (See Figure b).

1B Pull off the pen cap (See Figure c).

1C Check that the insulin is clear (See Figure d).

- Do not use the pen if the insulin looks cloudy, colored or contains particles.

1D Wipe the rubber seal with an alcohol swab (See Figure e).

If you have other injector pens:

- Making sure you have the correct medicine is especially important if you have other injector pens.

Step 2: Attach a new needle

- Do not reuse needles. Always use a new sterile needle for each injection. This helps stop blocked needles, contamination, and infection.

Only use needles that are compatible for use with Insulin Glargine-yfgn, such as Embecta Ultra fine

2A Take a new needle and peel off the protective seal (See Figure f).

2B Keep the needle straight and screw it onto the pen until fixed. Do not over-tighten (See Figure g).

2C Pull off the outer needle cap (See Figure h). Keep this for later.

2D Pull off the inner needle cap and throw away (See Figure i).

Handling needles

- Take care when handling needles to prevent needle-stick injury and cross-infection.

Step 3: Do a safety test

Always do a safety test before each injection to:

- Check your pen and the needle to make sure they are working properly.
- Make sure that you get the correct Insulin Glargine-yfgn dose.

3A Select 2 units by turning the dose selector until the dose pointer is at the 2 mark (See Figure j).

3B Press the injection button all the way in (See Figure k).

When insulin comes out of the needle tip, your pen is working correctly.

If no insulin appears:

- You may need to repeat this step up to 3 times before seeing insulin.
- If no insulin comes out after the third time, the needle may be blocked. If this happens:
  - change the needle (see Step 6 and Step 2),
  - then repeat the safety test (Step 3).
  - Do not use your pen if there is still no insulin coming out of the needle tip. Use a new pen.
  - Do not use a syringe to remove insulin from your pen.

If you see air bubbles:

- You may see air bubbles in the insulin. This is normal, they will not harm you.

Step 4: Select the dose

Do not select a dose or press the injection button without a needle attached. This may damage your pen.

4AMake sure a needle is attached and the dose is set to “0” (See Figure l).

4B Turn the dose selector until the dose pointer lines up with your dose (See Figure m).

- If you turn past your dose, you can turn back down.
- If there are not enough units left in your pen for your dose, the dose selector will stop at the number of units left.
- If you cannot select your full prescribed dose, use a new pen or inject the remaining units and use a new pen to complete your dose.

How to read the dose window

Even numbers are shown in line with dose pointer (See Figure n).

Odd numbers are shown as a line between even numbers (See Figure o).

Units of Insulin Glargine-yfgn in your pen:

- Your pen contains a total of 300 units of Insulin Glargine-yfgn. You can select doses from 1 to 80 units in steps of 1 unit. Each pen contains more than 1 dose.
- You can see roughly how many units of insulin are left by looking at where the plunger is on the insulin scale.

Step 5: Injecting Your Insulin Glargine-yfgn Dose

If you find it hard to press the injection button in, do not force it as this may break your pen. See the section below for help.

- Choose a place to inject as shown in the section "Places to Inject"
- Push the needle into your skin as shown by your healthcare provider (See Figure p).

Do not touch the injection button yet.

5C Place your thumb on the injection button. Slowly press all the way in and hold (see Figure q). Do not press hard.

- Do not press at an angle. Your thumb could block the dose selector from turning.

5D Keep the injection button held in and when you see "0" in the dose window, slowly count to 10 (See Figure r).

- This will make sure you get your full dose.

5E After holding and slowly counting to 10, release the injection button. Then remove the needle from your skin.

If you find it hard to press the button in:

- Change the needle (see Step 6 and Step 2) then do a safety test (see Step 3).
- If you still find it hard to press in, get a new pen.
- Do not use a syringe to remove insulin from your pen.

Step 6: Remove the needle

- Take care when handling needles to prevent needle-stick injury and cross-infection.
- Do not put the inner needle cap back on.

6A Grip the widest part of the outer needle cap. Keep the needle straight and guide it into the outer needle cap. Then push firmly on (See Figure s).

• The needle can puncture the cap if it is recapped at an angle.

6B Grip and squeeze the widest part of the outer needle cap. Turn your pen several times with your other hand to remove the needle (See Figure t).

- Try again if the needle does not come off the first time.

6C Throw away the used needle in a puncture-resistant container (see “Throwing your pen away” at the end of this Instructions for Use). (See Figure u).

6D Put your pen cap back on (See Figure v).

- Do not put the pen back in the refrigerator.

Storing the Insulin Glargine-yfgn Pen

Before first use:
• Keep new pens in the refrigerator between 36°F to 46°F (2°C to 8°C).
• Do not freeze. Do not use Insulin Glargine-yfgn if it has been frozen.

After first use:

• Keep your pen at room temperature below 86°F (30°C).
• Keep your pen away from heat or light.
• Store your pen with the pen cap on.
• Do not put your pen back in the refrigerator.
• Do not store your pen with the needle attached
• Keep out of the reach of children.
• Only use your pen for up to 28 days after its first use. Throw away the Insulin Glargine-yfgn pen you are using after 28 days, even if it still has insulin left in it.

Caring for Your Insulin Glargine-yfgn Pen

Handle your pen with care

• Do not drop your pen or knock it against hard surfaces.
• If you think that your pen may be damaged, do not try to fix it. Use a new one.

Protect your pen from dust and dirt

You can clean the outside of your pen by wiping it with a damp cloth (water only). Do not soak, wash or lubricate your pen. This may damage it.

Throwing your Pen away

- The used Insulin Glargine-yfgn pen may be thrown away in your household trash after you have removed the needle.
- Put the used needle in an FDA-cleared sharps disposal container right away after use. Do not throw away (dispose of) the used needles in your household trash.
- If you do not have an FDA-cleared sharps disposal container, you may use a household container that is:
  — made of a heavy-duty plastic,
  — can be closed with a tight-fitting, puncture-resistant lid, without sharps being able to come out,
  — upright and stable during use,
  — leak-resistant, and
  — properly labeled to warn of hazardous waste inside the container.

- When your sharps disposal container is almost full, you will need to follow your community guidelines for the right way to dispose of your sharps disposal container. There may be state or local laws about how you should throw away used needles and syringes. For more information about safe sharps disposal, and for specific information about sharps disposal in the state that you live in, go to the FDA’s website at: http://www.fda.gov/safesharpsdisposal.
- Do not dispose of your used sharps disposal container in your household trash unless your community guidelines permit this. Do not recycle your used sharps disposal container.

This Instructions for Use has been approved by the U.S. Food and Drug Administration.

Revised: 07/2025

Distributed by:

Civica, Inc.

Lehi, Utah 84048

Manufactured by:

Biocon Biologics Inc.

245 Main St, 2nd Floor

Cambridge, MA 02142 U.S.A

U.S. License No. 2324

Product of Malaysia

PRINCIPAL DISPLAY PANEL – 100 units/mL Pen

NDC 72572-422-05

Rx only

Insulin Glargine-yfgn

Injection
For Single Patient Use Only

100 units/mL (U-100)

For subcutaneous use only

Dispense in this sealed carton

Do not mix with other insulins

Use only if solution is clear and colorless with no particles visible

*Needles not included (see top panel)

Five 3 mL Prefilled Pens

Rx only

Each mL contains 100 units of insulin glargine-yfgn, and inactive ingredients: glycerol (20 mg), metacresol (2.7 mg), zinc chloride (content adjusted to provide 30 mcg zinc ion), and Water for Injection, USP. The pH is approximately 4. The pH is adjusted by addition of aqueous solutions of hydrochloric acid and/or sodium hydroxide.

Recommended dosage: see Prescribing Information.

As with any drug, if you are pregnant or nursing a baby, seek professional advice when using this product. Any change of insulin should be made cautiously and only under medical supervision.

Storage: Refrigerate at 2º to 8ºC (36º to 46ºF) until first use. Avoid freezing. Discard if frozen. After first use of a insulin glargine-yfgn pen, store the pen at room temperature (up to 30ºC [86ºF]) and discard after 28 days. Protect from direct heat and light.

WARNING: Keep this and all medication out of the reach of children.

Use within 28 days after initial use.

Initial Use Date:

Pen 1: _____ / _____ / ______.

Pen 2: _____ / _____ / ______.

Pen 3: _____ / _____ / ______.

Pen 4: _____ / _____ / ______.

Pen 5: _____ / _____ / ______.

Embecta Ultra-Fine needles are compatible with insulin glargine injection. These are sold separately and manufactured by embecta.

Copyright © 2025 Biocon Biologics Inc. All rights reserved.

Distributed by:

Civica, Inc.

Lehi, Utah 84048

Manufactured by:
Biocon Biologics Inc.
245 Main St, 2nd Floor,
Cambridge, MA 02142, U.S.A.
U.S. License No. 2324
Product of Malaysia

5's Carton Label